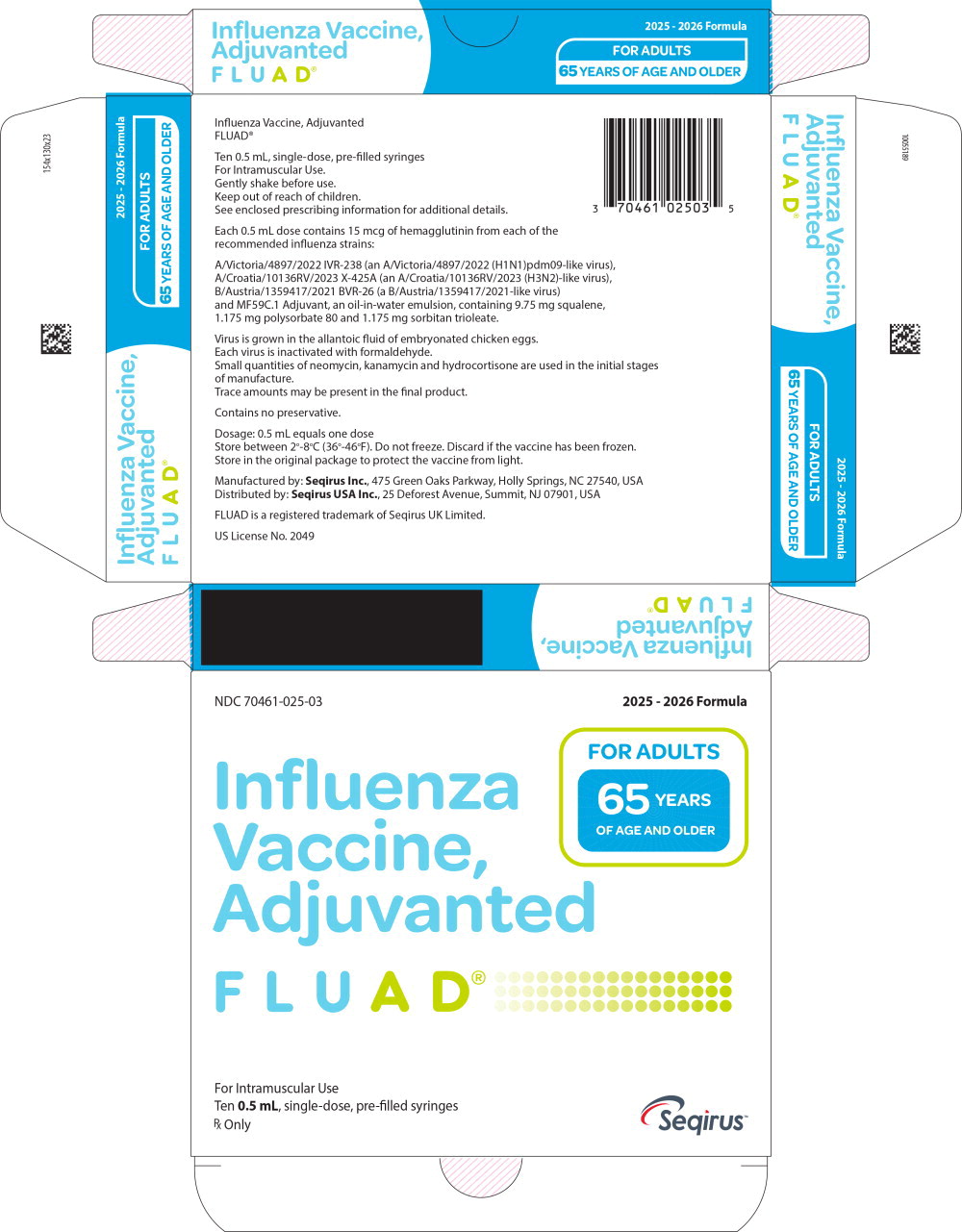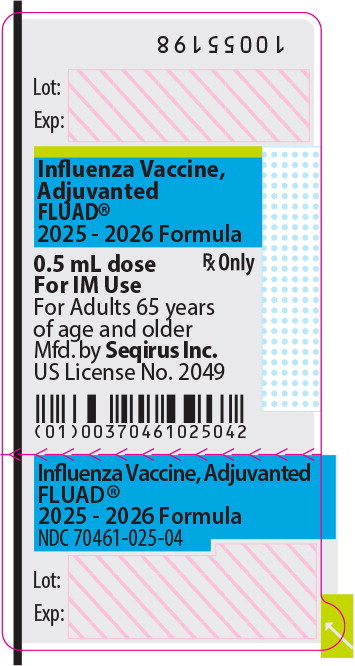 DRUG LABEL: FLUAD
NDC: 70461-025 | Form: INJECTION, SUSPENSION
Manufacturer: Seqirus, Inc.
Category: other | Type: VACCINE LABEL
Date: 20250701

ACTIVE INGREDIENTS: INFLUENZA A VIRUS A/VICTORIA/4897/2022 IVR-238 (H1N1) ANTIGEN (FORMALDEHYDE INACTIVATED) 15 ug/0.5 mL; INFLUENZA A VIRUS A/CROATIA/10136RV/2023 X-425A (H3N2) ANTIGEN (FORMALDEHYDE INACTIVATED) 15 ug/0.5 mL; INFLUENZA B VIRUS B/AUSTRIA/1359417/2021 BVR-26 ANTIGEN (FORMALDEHYDE INACTIVATED) 15 ug/0.5 mL
INACTIVE INGREDIENTS: sodium chloride; potassium chloride; potassium phosphate, monobasic; sodium phosphate, dibasic, dihydrate; magnesium chloride; calcium chloride; citric acid monohydrate; sorbitan trioleate; trisodium Citrate dihydrate; water; squalene; polysorbate 80

HIGHLIGHTS OF PRESCRIBING INFORMATION

These highlights do not include all the information needed to use FLUAD® safely and effectively. See full prescribing information for FLUAD.
FLUAD (Influenza Vaccine, Adjuvanted)
Injectable Emulsion for Intramuscular Use
2025-2026 Formula
Initial U.S. Approval: 2015

1 INDICATIONS AND USAGE

FLUAD is a vaccine indicated for active immunization for the prevention of influenza disease caused by influenza virus subtypes A and type B contained in the vaccine. FLUAD is approved for use in adults 65 years of age and older. (1)

This indication is approved under accelerated approval based on the immune response elicited by FLUAD (1). Continued approval for this indication may be contingent upon verification and description of clinical benefit in a confirmatory trial.

2 DOSAGE AND ADMINISTRATION

For intramuscular use

A single 0.5 mL dose for intramuscular injection. (2.1)

3 DOSAGE FORMS AND STRENGTHS

FLUAD is an injectable emulsion. A single dose is 0.5 mL. (3)

4 CONTRAINDICATIONS

Do not administer FLUAD to anyone with a history of a severe allergic reaction (e.g. anaphylaxis) to any component of the vaccine, including egg protein, or to a previous influenza vaccine. (4, 11)

5 WARNINGS AND PRECAUTIONS

If Guillain-Barré Syndrome (GBS) has occurred within six weeks of previous influenza vaccination, the decision to give FLUAD should be based on careful consideration of the potential benefits and risks. (5.1)

6 ADVERSE REACTIONS

The most common (≥10%) local and systemic adverse reactions in adults 65 years of age and older who received FLUAD were injection site pain (25%), injection site tenderness (21%), myalgia (15%), fatigue (13%) and headache (13%). (6)

To report SUSPECTED ADVERSE REACTIONS, contact Seqirus at 1-855-358-8966 or VAERS at 1-800-822-7967 and www.vaers.hhs.gov.

FULL PRESCRIBING INFORMATION

1 INDICATIONS AND USAGE

FLUAD is a vaccine indicated for active immunization for the prevention of influenza disease caused by influenza virus subtypes A and type B contained in the vaccine. FLUAD is approved for use in adults 65 years of age and older.

This indication is approved under accelerated approval based on the immune response elicited by FLUAD [see Clinical Studies (14)]. Continued approval for this indication may be contingent upon verification and description of clinical benefit in a confirmatory trial.

2 DOSAGE AND ADMINISTRATION

For intramuscular use

2.1 Dosage and Schedule

Administer FLUAD as a single 0.5 mL intramuscular injection in adults 65 years of age and older.

2.2 Administration

- Gently shake each syringe. FLUAD has a milky-white appearance. Parenteral drug products should be inspected visually for particulate matter and discoloration prior to administration whenever solution and container permit [see Description (11)]. If either condition exists, FLUAD should not be administered.
- To use a pre-filled syringe fitted with a Luer Lok system, remove the tip cap by unscrewing it in a counter-clockwise direction. Once the tip cap is removed, attach a needle to the syringe by screwing it on in a clockwise direction until it locks. Once the needle is locked in place, remove the needle protector and administer the vaccine.

3 DOSAGE FORMS AND STRENGTHS

FLUAD is an injectable emulsion. A single dose is 0.5 mL.

4 CONTRAINDICATIONS

Do not administer FLUAD to anyone with a history of a severe allergic reaction (e.g., anaphylaxis) to any component of the vaccine, including egg protein [see Description (11)], or to a previous influenza vaccine.

5 WARNINGS AND PRECAUTIONS

5.1 Guillain-Barré Syndrome

If Guillain-Barré syndrome (GBS) has occurred within 6 weeks of receipt of prior influenza vaccine, the decision to give FLUAD should be based on careful consideration of the potential benefits and risks.

The 1976 swine influenza vaccine was associated with an elevated risk of GBS. [see References (1)] Evidence for a causal relationship of GBS with other influenza vaccines is inconclusive; if an excess risk exists, it is probably slightly more than 1 additional case per 1 million persons vaccinated.

5.2 Preventing and Managing Allergic Reactions

Appropriate medical treatment must be immediately available to manage potential anaphylactic reactions following administration of FLUAD.

5.3 Altered Immunocompetence

The immune response to FLUAD in immunocompromised persons, including individuals receiving immunosuppressive therapy, may be lower than in immunocompetent individuals.

5.4 Syncope

Syncope (fainting) may occur in association with administration of injectable vaccines including FLUAD. Procedures should be in place to avoid injury from fainting.

5.5 Limitations of Vaccine Effectiveness

Vaccination with FLUAD may not protect all vaccine recipients against influenza disease.

6 ADVERSE REACTIONS

The most common (≥10%) local and systemic adverse reactions in adults 65 years of age and older who received FLUAD were injection site pain (25%), injection site tenderness (21%), myalgia (15%), fatigue (13%) and headache (13%).

6.1 Clinical Trials Experience

Because clinical trials are conducted under widely varying conditions, the adverse reaction rates observed in the clinical trials of a vaccine cannot be directly compared to rates in the clinical trials of another vaccine and may not reflect rates observed in clinical practice.

The safety of FLUAD and FLUAD QUADRIVALENT was evaluated in 17 clinical studies in 10,911 adults 65 years of age and older. Data for FLUAD QUADRIVALENT are relevant to FLUAD because both vaccines are manufactured using the same process and have overlapping compositions.

Study 1 (NCT01162122) was a multicenter, observer-blind, randomized controlled study conducted in the United States, Colombia, Panama and the Philippines during the 2010-2011 Northern Hemisphere influenza season. The safety analysis set included 3545 FLUAD recipients and 3537 AGRIFLU (Influenza Vaccine) recipients. The enrolled subject population was 65 to 97 years of age (mean 72 years) and 64% were female. Within each treatment group, 53% were Asian, 28% were Caucasian, 18% were Hispanic, 1% were Black, and fewer than 1% each were Native American/Alaskan, Pacific Islander/Hawaiian, or Other.

Solicited local (injection site) and systemic adverse reactions were collected from subjects who completed a symptom diary card for seven days following vaccination. The reported frequencies of solicited local adverse reactions are presented in Table 1a and systemic adverse reactions are presented in Table 1b.

Table 1a: Percentages of Subjects ≥ 65 Years of Age With Solicited Local Adverse Reactions in Days 1-7 After Administration of FLUAD or AGRIFLU (a U.S. Licensed Comparator) NCT01162122
Solicited Local Adverse Reactions | FLUAD (Na=3418-3496) Percentage | AGRIFLU (Na=3420-3488) Percentage
Injection site Pain: Any | 25.0 | 12.2
Injection site Pain: Moderateb | 3.9 | 1.9
Injection site Pain: Severec | 0.3 | 0.2
Tenderness: Any | 21.1 | 11.2
Tenderness: Moderate | 3.0 | 1.0
Tenderness: Severe | 0.1 | 0.2
Erythema: Any | 1.2 | 0.5
Erythema: 25 to ≤ 50 mm | 1.1 | 0.5
Erythema: 51 to ≤ 100 mm | 0.2 | <0.1
Erythema: > 100 mm | 0.0 | 0.0
Induration: Any | 1.3 | 0.5
Induration: 25 to ≤ 50 mm | 1.0 | 0.5
Induration: 51 to ≤ 100 mm | 0.3 | 0.0
Induration: > 100 mm | 0.0 | 0.0
Swelling: Any | 1.2 | 0.4
Swelling: 25 to ≤ 50 mm | 1.0 | 0.4
Swelling: 51 to ≤ 100 mm | 0.2 | <0.1
Swelling: > 100 mm | <0.1 | 0.0
a N = number of subjects with safety data.
b Moderate: pain, tenderness, defined as “some limitation in normal daily activity”
c Severe: pain, tenderness, defined as “unable to perform normal daily activity”

Table 1b: Percentages of Subjects ≥ 65 Years of Age With Solicited Systemic Adverse Reactions in Days 1-7 After Administration of FLUAD or AGRIFLU (a U.S. Licensed Comparator) NCT01162122
Solicited Systemic Adverse Reactions | FLUAD (Na=3418-3496) Percentage | AGRIFLU (Na=3420-3488) Percentage
Myalgia: Any | 14.7 | 9.7
Myalgia: Moderateb | 2.6 | 1.8
Myalgia: Severec | 0.3 | 0.7
Fatigue: Any | 13.3 | 10.4
Fatigue: Moderate | 3.1 | 2.4
Fatigue: Severe | 0.4 | 0.6
Fatigue: PLTd | 0.0 | <0.1
Headache: Any | 13.2 | 11.2
Headache: Moderate | 3.0 | 2.6
Headache: Severe | 0.4 | 0.6
Headache: PLT | 0.0 | <0.1
Arthralgia: Any | 8.5 | 7.8
Arthralgia: Moderate | 1.6 | 1.6
Arthralgia: Severe | 0.2 | 0.6
Chills: Any | 6.7 | 4.7
Chills: Moderate | 1.5 | 1.2
Chills: Severe | 0.3 | 0.3
Chills: PLT | <0.1 | 0.0
Diarrhea: Any | 4.8 | 4.5
Diarrhea: Moderate | 1.3 | 0.9
Diarrhea: Severe | 0.3 | 0.2
Diarrhea: PLT | <0.1 | <0.1
Fever: Any | 3.6 | 3.4
Fever: ≥38.0°C to ≤ 38.4°C | 1.8 | 1.7
Fever: ≥ 38.5°C to ≤ 38.9°C | 1.3 | 1.3
Fever: 39.0°C to ≤ 40.0°C | 0.4 | 0.4
Fever: ≥ 40.0°C | 0.1 | 0.0
Nausea: Any | 2.9 | 2.8
Nausea: Moderate | 0.4 | 0.6
Nausea: Severe | 0.1 | 0.1
Nausea: PLT | <0.1 | 0.0
Vomiting: Any | 1.4 | 1.7
Vomiting: Moderate | 0.4 | 0.5
Vomiting: Severe | <0.1 | 0.1
Vomiting: PLT | <0.1 | 0.0
a N = number of subjects with safety data.
b Moderate: myalgia, fatigue, headache, arthralgia, chills, nausea, vomiting defined as “some limitation in normal daily activity”, diarrhea defined as “4 to 5 stools a day”.
c Severe: myalgia, fatigue, headache, arthralgia, chills, nausea, vomiting defined as “unable to perform normal daily activity”, diarrhea defined as “6 or more watery stools a day”.
d Potentially life threatening (PLT) reaction defined as requiring emergency room visit or hospitalization.

Unsolicited Adverse Events (AEs): The clinical safety of FLUAD was assessed in fifteen (15) randomized, controlled studies. The total safety population in these trials included 10,952 adults 65 years of age and older, comprising 5,754 who received FLUAD and 5,198 who received other US licensed influenza vaccines. The percentage of subjects with an unsolicited AE within 30 days following vaccination was similar between vaccine groups (16.9% FLUAD vs. 18.0% active comparator).

Serious Adverse Events (SAEs) and Deaths: In Study 1, in which subjects were followed for SAEs and deaths for one year following vaccination (N=3,545 FLUAD, N=3,537 AGRIFLU), the percentages of subjects with an SAE were similar between vaccine groups (7% FLUAD vs. 7% AGRIFLU). Four SAEs (1 FLUAD and 3 AGRIFLU) were assessed as related to study vaccination over one year of observation and 2 of these occurred (1 FLUAD and 1 AGRIFLU) within 21 days following study vaccination. There were 98 deaths (N=52 FLUAD, N=46 AGRIFLU) over one year of which none occurred within the first 21 days following vaccination.

In 14 additional randomized, controlled studies, SAEs were collected over a 3 to 4-week period in 4 studies, over a 8-week period in 1 study, and over a 6-month period in 9 studies (N= 2,209 FLUAD, N=1,661 US licensed influenza vaccines). The percentages of subjects with an SAE within 30 days (1.1% FLUAD vs. 1.8% AGRIFLU) or within 6 months (4.3% FLUAD vs. 5.9% AGRIFLU) were similar between vaccine groups. The percentages of deaths within 30 days (0.3% FLUAD vs. 0.6% active comparator) or within 6 months (1.0% FLUAD vs. 1.5% active comparator) were also similar.

Adverse Events of Special Interest (AESIs): Rates of new onset neuroinflammatory and immune mediated diseases were assessed in a post hoc analysis of the 15 randomized controlled studies over the time periods specified above for SAEs. The percentage of subjects with an AESI at any time after vaccination was similar between vaccine groups (0.9% FLUAD vs. 0.9% active comparator). There were no notable imbalances for specific AESIs.

Safety of Annual Revaccination: In 5 of the randomized, controlled trials, subjects were followed for SAEs and deaths for 6 months following revaccination (N=492 FLUAD, N=330 US licensed and non-US licensed influenza vaccines). After the second annual vaccination, the percentages of subjects with an SAE were similar between vaccine groups (6.1% FLUAD vs.

5.5% comparator influenza vaccines); 23 deaths (N=17 FLUAD, N=6 comparator influenza vaccines) were reported. Causes of death included cardiovascular events, malignancy, trauma, gastrointestinal disorders, and respiratory failure. Clinical characteristics of the deaths, including the variable causes, timing since vaccination, and underlying medical conditions, do not provide evidence for a causal relationship with FLUAD.

Safety of FLUAD QUADRIVALENT

Study 2 (NCT02587221) was a multi-center, randomized, observer-blind, non-influenza comparator-controlled efficacy and safety study conducted in 12 countries during the 2016-2017 Northern Hemisphere and 2017 Southern Hemisphere seasons. In this study, 3381 subjects received FLUAD QUADRIVALENT and 3380 subjects received a US-licensed non-influenza comparator vaccine (Tetanus Toxoid, Reduced Diphtheria Toxoid and Acellular Pertussis Vaccine, Boostrix® [GlaxoSmithKline Biologicals]).

Serious adverse events (SAEs) and potentially immune-mediated adverse events of special interest (AESIs) were collected up to 366 days after vaccination. SAEs were reported by 238 (7.0%) FLUAD QUADRIVALENT recipients and 234 (6.9%) comparator recipients. There were no SAEs, AESIs or deaths in this study that were related to FLUAD QUADRIVALENT.

Study 3 (NCT03314662) was a multicenter, randomized, double-blind, comparator-controlled study conducted during the 2017-18 Northern Hemisphere influenza season. In this study, 888 subjects received FLUAD QUADRIVALENT, 444 subjects received FLUAD (aTIV-1) and 444 subjects received FLUAD (aTIV-2). FLUAD (aTIV-1) contained hemagglutinin from a Type B virus of the Victoria lineage, and FLUAD (aTIV-2) contained hemagglutinin from a Type B virus of the Yamagata lineage.

Serious AEs and AESIs were collected up to 181 days after vaccination. Within 6 months after vaccination, 37 (4.2%) FLUAD QUADRIVALENT recipients, 28 (6.3%) FLUAD (aTIV-1) and 18 (4.1%) FLUAD (aTIV-2) recipients experienced an SAE. There were no SAEs, AESIs or deaths in this study that were related to the study vaccine. There were no AEs leading to withdrawal from the study.

6.2 Postmarketing Experience

In addition to the adverse reactions observed during clinical trials, the following adverse events were reported from postmarketing surveillance in individuals 65 years of age and older for FLUAD or FLUAD QUADRIVALENT. Data for FLUAD QUADRIVALENT are relevant to FLUAD because both vaccines are manufactured using the same process and have overlapping compositions. Because these events were reported voluntarily from a population of uncertain size, it is not possible to reliably estimate their frequency or to establish, for all events, a causal relationship to vaccine exposure.

Blood and lymphatic system disorders:

Thrombocytopenia (some cases were severe with platelet counts less than 5,000 per mm^3), lymphadenopathy

Immune system disorders:

Allergic reactions including anaphylactic shock (in rare cases), anaphylaxis

Nervous system disorders:

Encephalomyelitis, Guillain-Barré Syndrome, convulsions, neuritis, neuralgia, paresthesia, syncope, presyncope, dizziness

Vascular disorders:

Vasculitis which may be associated with transient renal involvement

Skin and subcutaneous tissue disorders:

Generalized skin reactions including erythema multiforme, urticaria, pruritis or non-specific rash, erythema, angioedema

Musculoskeletal and connective tissue disorders:

Muscular weakness, pain in extremity

General disorders and administration site conditions:

Extensive swelling of injected limb, injection site cellulitis-like reaction, injection site swelling, peripheral swelling, asthenia, malaise, pyrexia

8 USE IN SPECIFIC POPULATIONS

Data for FLUAD QUADRIVALENT are relevant to FLUAD because both vaccines are manufactured using the same process and have overlapping compositions.

8.1 Pregnancy

Risk Summary

FLUAD is not approved for use in persons < 65 years of age.

All pregnancies have a risk of birth defect, loss, or other adverse outcomes. In the U.S. general population, the estimated background risk of major birth defects and miscarriage in clinically recognized pregnancies is 2% to 4% and 15% to 20%, respectively. The data are insufficient to establish if there is vaccine-associated risk with FLUAD in pregnant women.

A developmental toxicity study was performed in female rabbits administered FLUAD prior to mating and during gestation. A 0.5 mL dose was injected on each occasion (a single human dose is 0.5 mL). Animals were administered FLUAD by intramuscular injection twice prior to gestation, during the period of organogenesis (gestation day 7) and later in pregnancy (gestation day 20), 0.5 mL (45 mcg)/rabbit/occasion. No vaccine-related fetal malformations or variations and no adverse effects on pre-weaning development were observed in the study. FLUAD did not affect female fertility in the rabbit developmental toxicity study.

8.2 Lactation

Risk Summary

FLUAD is not approved for use in persons < 65 years of age. It is not known whether FLUAD is excreted in human milk. Data are not available to assess the effects of FLUAD on the breastfed infant or on milk production/excretion. The developmental and health benefits of breastfeeding should be considered along with the mother's clinical need for FLUAD and any potential adverse effects on the breastfed child from FLUAD or from the underlying maternal condition. For preventive vaccines, the underlying maternal condition is susceptibility to disease prevented by the vaccine.

8.3 Pediatric Use

Safety and effectiveness of FLUAD and FLUAD QUADRIVALENT were evaluated in clinical trials conducted in children 6 months to <72 months of age. Data for FLUAD QUADRIVALENT are relevant to FLUAD because both vaccines are manufactured using the same process and have overlapping compositions. Data from these trials are inconclusive to demonstrate the safety and effectiveness of FLUAD in children 6 months to <72 months of age. The safety and effectiveness of FLUAD in infants less than 6 months of age and in children older than 72 months of age have not been evaluated.

8.4 Geriatric Use

Safety and immunogenicity of FLUAD have been evaluated in adults 65 years of age and older. [See Adverse Reactions (6.1) and Clinical Studies (14)]

11 DESCRIPTION

FLUAD (Influenza Vaccine, Adjuvanted), a sterile injectable emulsion for intramuscular use, is a trivalent inactivated influenza vaccine prepared from virus propagated in the allantoic cavity of embryonated hens' eggs inoculated with a specific type of influenza virus.

FLUAD is standardized according to United States Public Health Service requirements and each 0.5 mL dose is formulated to contain 15 mcg of hemagglutinin (HA) from each of the following influenza strains recommended for the 2025-2026 influenza season: A/Victoria/4897/2022 IVR-238 (an A/Victoria/4897/2022 (H1N1)pdm09-like virus), A/Croatia/10136RV/2023 X-425A (an A/Croatia/10136RV/2023 (H3N2)-like virus), B/Austria/1359417/2021 BVR-26 (a B/Austria/1359417/2021-like virus). FLUAD also contains MF59C.1 adjuvant (MF59®), a squalene based oil-in-water emulsion. Each of the strains is harvested and clarified separately by centrifugation and filtration prior to inactivation with formaldehyde. The inactivated virus is concentrated and purified by zonal centrifugation. The surface antigens, hemagglutinin and neuraminidase, are obtained from the influenza virus particle by further centrifugation in the presence of cetyltrimethylammonium bromide (CTAB). The antigen preparation is further purified.

FLUAD is prepared by combining the three virus antigens with the MF59C.1 adjuvant. After combining, FLUAD is a sterile, milky-white injectable emulsion supplied in single-dose pre-filled syringes containing 0.5 mL dose. Each 0.5 mL dose contains 15 mcg of hemagglutinin (HA) from each of the three recommended influenza strains and MF59C.1 adjuvant (9.75 mg squalene, 1.175 mg of polysorbate 80, 1.175 mg of sorbitan trioleate, 0.66 mg of sodium citrate dihydrate and 0.04 mg of citric acid monohydrate) at pH 6.9-7.7.

FLUAD may contain trace amounts of neomycin (≤ 0.02 mcg by calculation), kanamycin (≤ 0.03 mcg by calculation) and hydrocortisone (≤ 0.005 ng by calculation) which are used during the initial stages of manufacture, as well as residual egg protein (ovalbumin) (≤ 0.4 mcg), formaldehyde (≤ 10 mcg) or CTAB (≤ 12 mcg).

FLUAD does not contain a preservative. The syringe, syringe plunger stopper and tip caps are not made with natural rubber latex.

12 CLINICAL PHARMACOLOGY

Mechanism of Action

Specific levels of hemagglutination inhibition (HI) antibody titers induced by vaccination with inactivated influenza virus vaccine have not been correlated with protection from influenza illness. In some human studies, HI antibody titers of 1:40 or greater have been associated with protection from influenza illness in up to 50% of subjects. [see References (2,3)]

Antibody against one influenza virus type or subtype confers limited or no protection against another. Furthermore, antibody to one antigenic variant of influenza virus might not protect against a new antigenic variant of the same type or subtype. Frequent development of antigenic variants through antigenic drift is the virologic basis for seasonal epidemics and the reason for the usual change of one or more new strains in each year's influenza vaccine.

13 NONCLINICAL TOXICOLOGY

Carcinogenesis, Mutagenesis, Impairment of Fertility

FLUAD has not been evaluated for carcinogenic or mutagenic potential, or for impairment of male fertility in animals.

14 CLINICAL STUDIES

Study 1 (NCT01162122) evaluated the safety and immunogenicity of FLUAD in comparison to AGRIFLU. A total of 7082 subjects were randomized and vaccinated with FLUAD (N=3541) or AGRIFLU (N=3541). The primary immunogenicity analyses were conducted on all vaccinated subjects with a blood sample collected at Day 22 (N=3225-3227 [91%] and 3,256- 3,259 [92%] in the FLUAD and AGRIFLU groups, respectively). Non-inferiority of FLUAD compared with AGRIFLU was demonstrated for all three vaccine strains based on pre-defined thresholds for seroconversion rate differences and GMT ratios (Table 2a & 2b).

Table 2a: Immune Responses to Each Antigen 22 Days after Vaccination with FLUAD or AGRIFLU in Adults 65 Years and Oldera (Study 1)
GMTs Against FLUAD and AGRIFLU Vaccine Strains | FLUAD N b= 3225-3227 GMT (95% CI) | AGRIFLU Nb =3256-3259 GMT (95% CI) | FLUAD and AGRIFLU GMT Ratioc (95% CI)
A/California/7/2009-like (H1N1) | 99 (93-106) | 70 (66-75) | 1.4 (1.32-1.49)
A/Perth/16/2009-like (H3N2) | 272 (257-288) | 169 (159-179) | 1.61 (1.52-1.7)
B/Brisbane/60/2008- like | 28 (26-29) | 24 (23-26) | 1.15 (1.08-1.21)
GMT = Geometric mean antibody titer; CI = Confidence Interval.
a Results obtained following vaccination with influenza vaccine formulated for the 2010-2011 season.
b N is the number of vaccinated participants with available data for the immunologic endpoint listed.
c FLUAD met non-inferiority criteria based on GMT ratios if the lower limit of the 95% CI [FLUAD:AGRIFLU] for each strain was > 0.67.

Table 2b: Immune Responses to Each Antigen 22 Days after Vaccination with FLUAD or AGRIFLU in Adults 65 Years and Oldera (Study 1)
Seroconversionc for Vaccine Strains: | FLUAD Nb= 3225-3227 % of Subjects (95% CI) | AGRIFLU Nb =3256-3259 % of Subjects (95% CI) | FLUAD and AGRIFLU Difference in Seroconversion Rated (95% CI)
A/California/7/2009- like (H1N1) | 69% (67%–70%) | 58% (57%–60%) | 9.8% (7.5%–12.1%)
A/Perth/16/2009-like (H3N2) | 73% (71%–74%) | 58% (56%–60%) | 13.9% (11.7%–16.1%)
B/Brisbane/60/2008- like | 33% (31%–35%) | 29% (28%–31%) | 3.2% (1.1%–5.3%)
a Results obtained following vaccination with influenza vaccine formulated for the 2010-2011 season.
b N is the number of vaccinated participants with available data for the immunologic endpoint listed.
c Seroconversion was defined as prevaccination HI titer <10 and postvaccination HI titer ≥ 40 or at least a 4-fold increase in HI from prevaccination HI titer ≥ 10.
d FLUAD met non-inferiority criteria based on seroconversion rate differences if the lower limit of the 95% CI
[FLUAD -AGRIFLU] for each strain was >-10% .

15 REFERENCES

1. Lasky T, Terracciano GJ, Magder L, et al. The Guillain-Barre syndrome and the 1992-1993 and 1993-1994 influenza vaccines. N Engl J Med 1998; 339(25): 1797-1802.
2. Hannoun C, Megas F, Piercy J. Immunogenicity and protective efficacy of influenza vaccination. Virus Res 2004; 103:133-138.
3. Hobson D, Curry RL, Beare A, et. al. The role of serum hemagglutinin-inhibiting antibody in protection against challenge infection with influenza A2 and B viruses. J Hyg Camb 1972; 767-777.

16 HOW SUPPLIED/STORAGE AND HANDLING

FLUAD is supplied in the product presentation listed below:

Presentation | Carton NDC Number | Components
Pre-Filled Syringe | 70461-025-03 | 0.5 mL dose in a pre-filled syringe (needle not supplied), package of 10 syringes per carton [NDC 70461-025-04]

Store FLUAD refrigerated at 2°C to 8°C (36°F to 46°F). Protect from light. Do not freeze. Discard if the vaccine has been frozen. Do not use after expiration date.

The syringe, syringe plunger stopper and tip cap are not made with natural rubber latex.

17 PATIENT COUNSELING INFORMATION

- Inform vaccine recipients of the potential benefits and risks of immunization with FLUAD.
- Educate vaccine recipients regarding the potential side effects. Clinicians should emphasize that (1) FLUAD contains non-infectious particles and cannot cause influenza and (2) FLUAD is intended to help provide protection against illness due to influenza viruses only.
- Instruct vaccine recipients to report adverse reactions to their healthcare provider and/or to Vaccine Adverse Event Reporting System (VAERS) at 1-800-822-7967 and www.vaers.hhs.gov. Provide vaccine recipients with the Vaccine Information Statements which are required by the National Childhood Vaccine Injury Act of 1986. These materials are available free of charge at the Centers for Disease Control and Prevention (CDC) website (www.cdc.gov/vaccines).
- Inform vaccine recipients that annual vaccination is recommended.

FLUAD, FLUAD QUADRIVALENT and MF59 are registered trademarks of Seqirus UK Limited or its affiliates.

Manufactured by: Seqirus Inc., 475 Green Oaks Parkway, Holly Springs, NC 27540, USA

Distributed by: Seqirus USA Inc., 25 Deforest Avenue, Summit, NJ 07901, USA

Tel: 1-855-358-8966

US License No. 2049

Principal Display Panel – 0.5 mL Carton Label

NDC 70461-025-03

2025 - 2026 Formula

Influenza
Vaccine,
Adjuvanted
FLUAD®

FOR ADULTS
65 YEARS
OF AGE AND OLDER

For Intramuscular Use

Ten 0.5 mL, single-dose, pre-filled syringes

Rx Only

Seqirus™

Principal Display Panel – 0.5 mL Syringe Label

Influenza Vaccine,
Adjuvanted
FLUAD®

2025 - 2026 Formula

NDC 70461-025-04